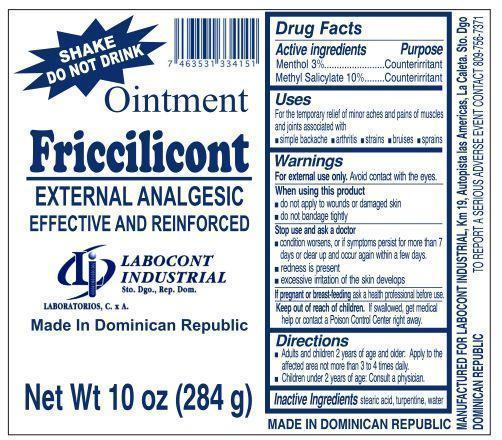 DRUG LABEL: Friccilicont
NDC: 53038-001 | Form: CREAM
Manufacturer: Labocont Industrial
Category: otc | Type: HUMAN OTC DRUG LABEL
Date: 20171221

ACTIVE INGREDIENTS: MENTHOL 3 g/100 g; METHYL SALICYLATE 10 g/100 g
INACTIVE INGREDIENTS: STEARIC ACID; TURPENTINE; WATER

Friccilicont Ointment

Active ingredients

Menthol 3%

Methyl Salicylate 10%

Purpose

Counterirritant

Counterirritant

Uses

For the temporary relief of minor aches and pains of muscles and joints associated with

simple backache
arthritis
strains
bruises
sprains

Warnings

For external use only. Avoid contact with the eyes.

When using this product

do not apply to wounds or damaged skin

do not bandage tightly

Stop use and ask a doctor

condition worsens, or if symptoms persist for more than 7
days or clear up and occur again within a few days

redness is present

excessive irritation of the skin develops

If pregnant or breast-feeding

ask a health professional before use.

Keep out of reach of children.

If swallowed, get medical help or contact a Poison Control Center right away.

Directions

Adults and children 2 years of age and older: Apply to the affected area not more than 3 to 4 times daily.

Children under 2 years of age: Consult a physician.

Inactive Ingredients

stearic acid, turpentine, water

PACKAGE LABEL

SHAKE
DO NOT DRINK

Ointment

Friccilicont
EXTERNAL ANALGESIC
EFFECTIVE AND REINFORCED

LABOCONT
INDUSTRIAL
Sto. Dgo., Rep. Dom.

LABORATORIOS, C. x A.

Made In Dominican Republic

Net Wt 10 oz (284 g)

MADE IN DOMINICAN REPUBLIC

MANUFACTURED FOR LABOCONT INDUSTRIAL, Km 19, Autopista las Americas, La Caleta. Sto. Dgo
DOMINICAN REPUBLIC TO REPORT A SERIOUS ADVERSE EVENT CONTACT 8109-756-7371